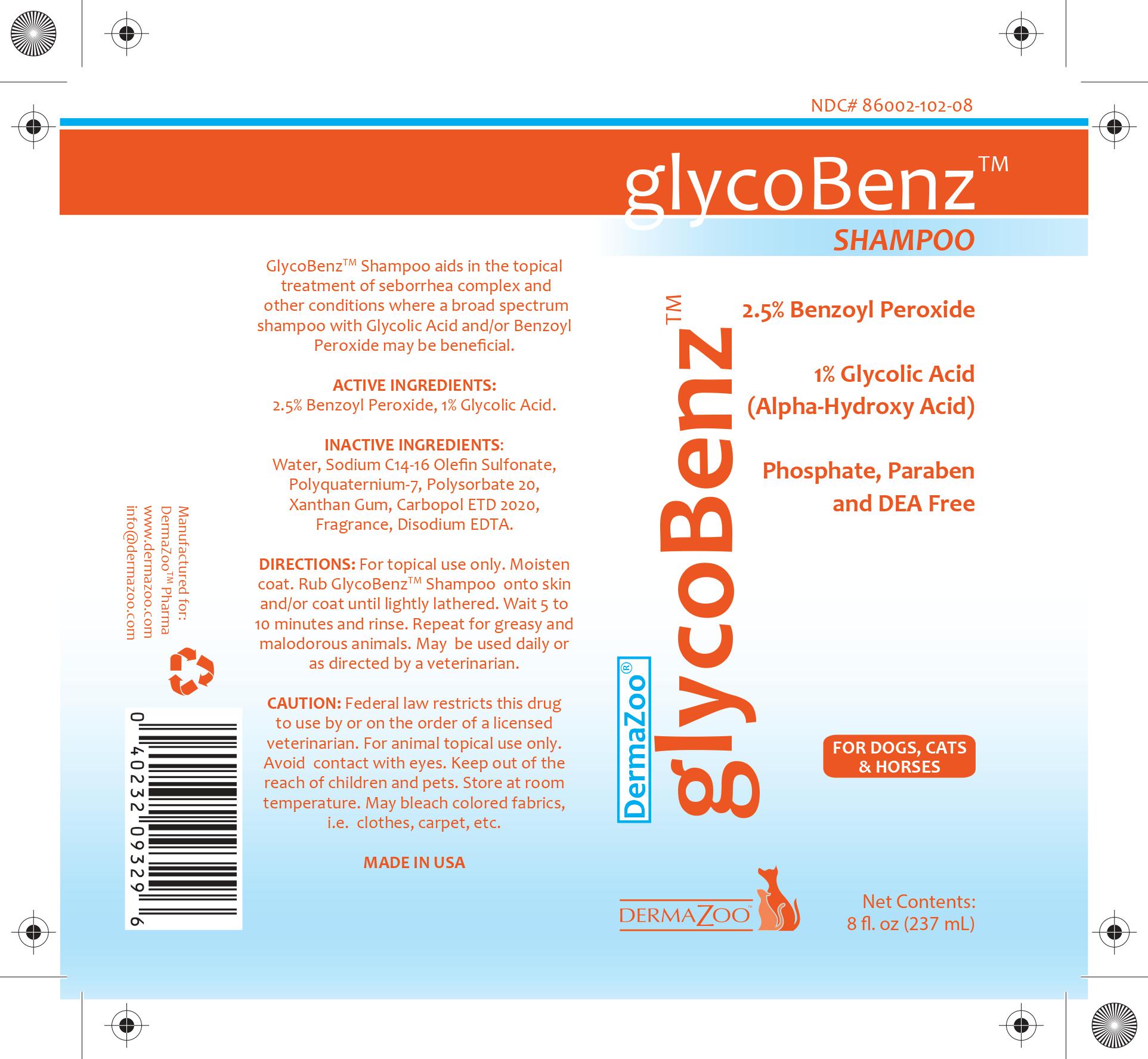 DRUG LABEL: GlycoBenz
NDC: 86002-102 | Form: SHAMPOO
Manufacturer: DermaZoo, LLC
Category: animal | Type: PRESCRIPTION ANIMAL DRUG LABEL
Date: 20240410

ACTIVE INGREDIENTS: Benzoyl Peroxide 2.5 g/1000 mL; GLYCOLIC ACID 1 g/1000 mL
INACTIVE INGREDIENTS: WATER; SODIUM C14-16 OLEFIN SULFONATE; POLYACRYLIC ACID (8000 MW); COCAMIDOPROPYL BETAINE; LAURAMINE OXIDE; METHYLCHLOROISOTHIAZOLINONE; METHYLISOTHIAZOLINONE

DERMAZOO - GLYCOBENZ (86002-102)

INDICATIONS AND USAGE

GlycoBenz™ Shampoo aids in the topical treatment of seborrhea complex and other conditions where a broad spectrum shampoo with Glycolic Acid and/or Benzoyl Peroxide may be beneficial.

DIRECTIONS: For topical use only. Moisten coat. Rub GlycoBenz™ Shampoo onto skin and/or coat until lightly lathered. Wait 5 to 10 minutes and rinse. Repeat for greasy and malodorous animals. May be used daily or as directed by a veterinarian.

DESCRIPTION

ACTIVE INGREDIENT: 2.5% Benzoyl Peroxide, 1% Glycolic Acid

INACTIVE INGREDIENTS: Water, Sodium C14-16 Alpha Olefin Sulfonate, Acrylates Copolymer, Cocamidopropyl Betaine, Lauramine Oxide, Fragrance, Methylchloroisothiazolinone, Methylisothiazolinone

WARNINGS AND PRECAUTIONS

CAUTION: Federal law restricts this drug to use by or on the order of a licensed veterinarian.

For animal topical use only. Avoid contact with eyes. Keep out of the reach of children and pets. Store at room temperature. May bleach colored fabrics, i.e. clothes, carpet, etc.

glycoBenz™

2.5% Benzoyl Peroxide

1% Glycolic Acid (Alpha-Hydroxy Acid)

Phosphate, Paraben, and DEA Free

For Dogs, Cats, and Horses

Net Contents: 8 fl. oz. (237 mL)

Made in USA

Manufactured for: DermaZoo™ Pharma, www.dermazoo.com, info@dermazoo.com